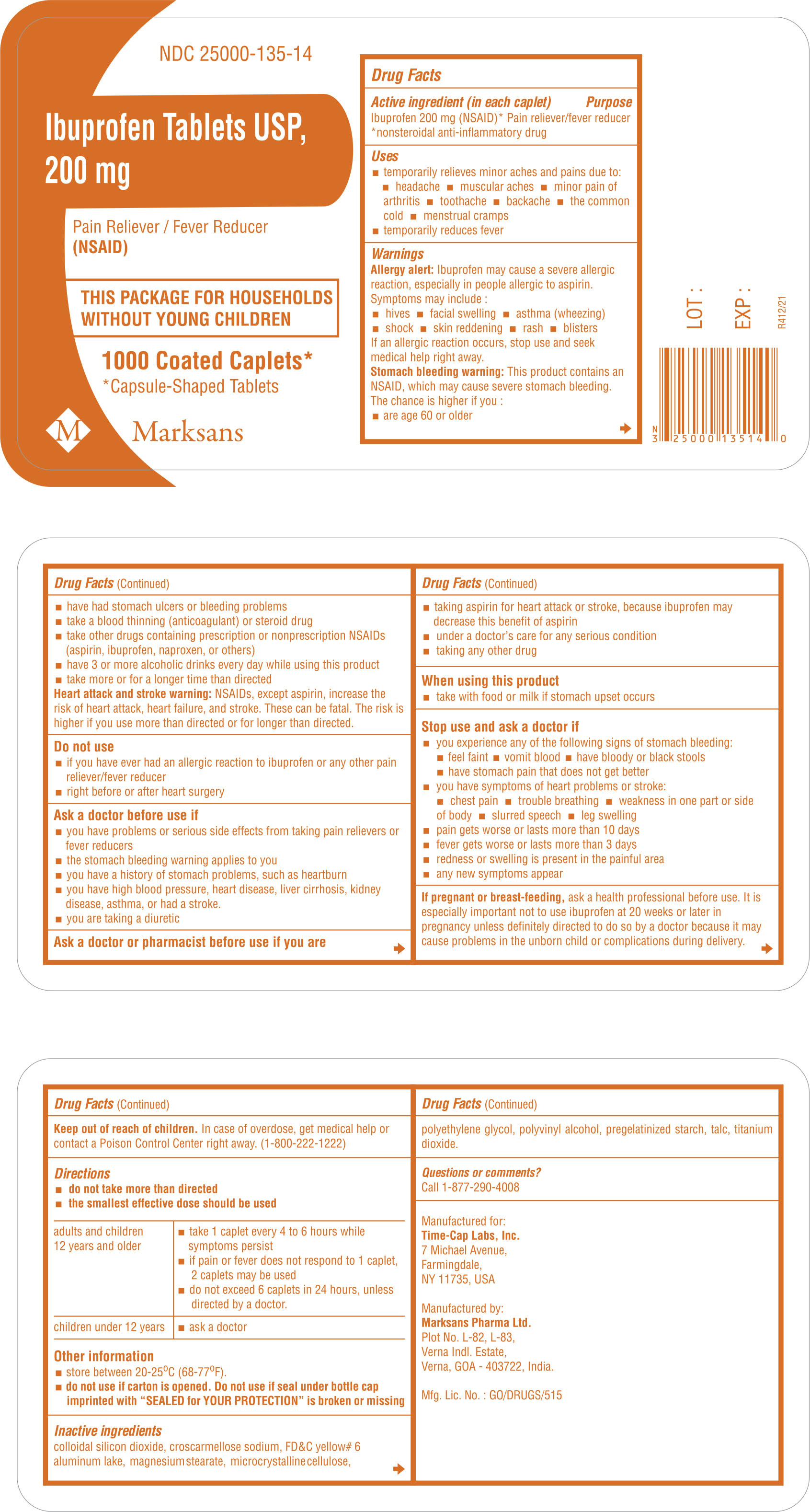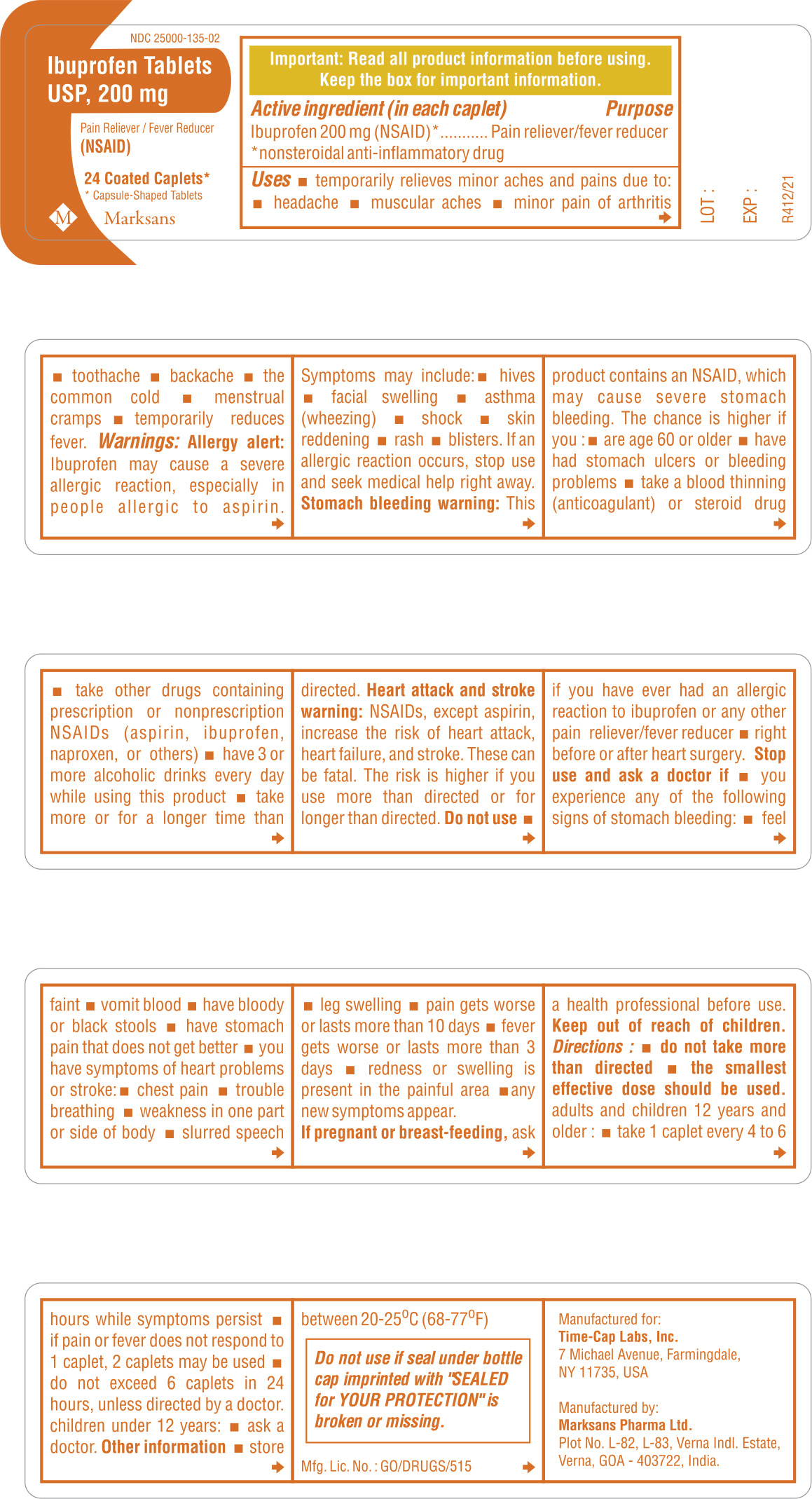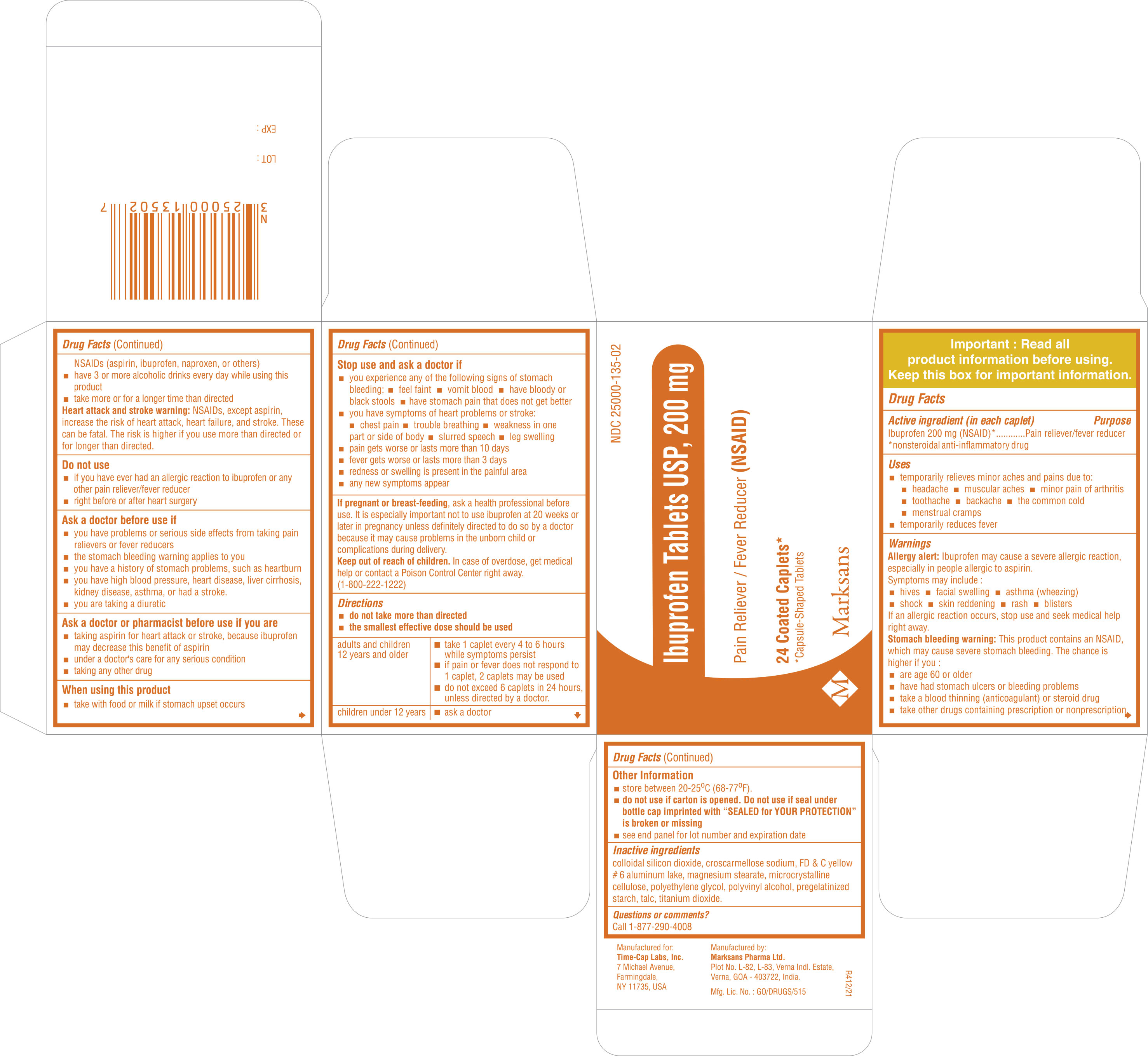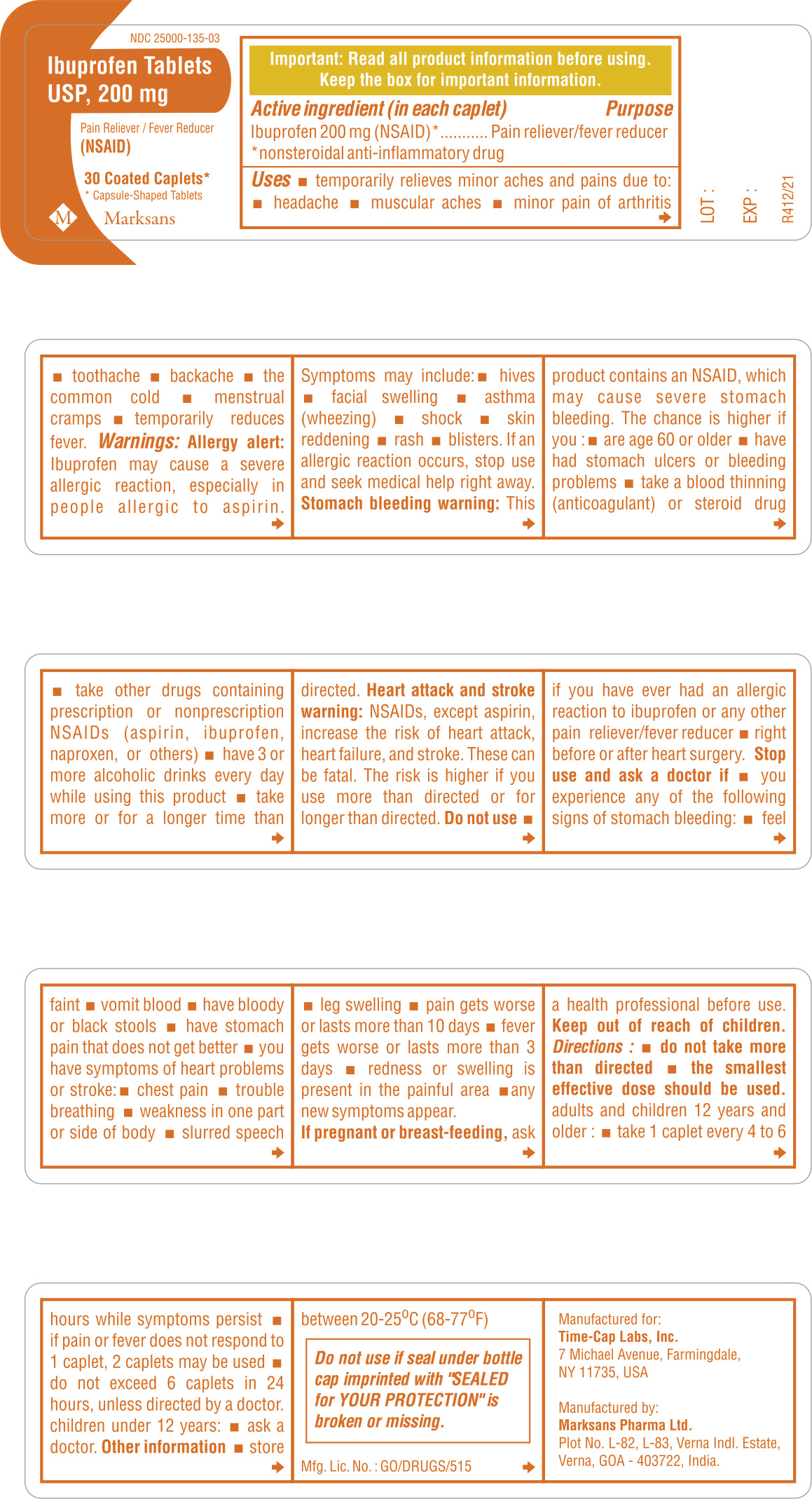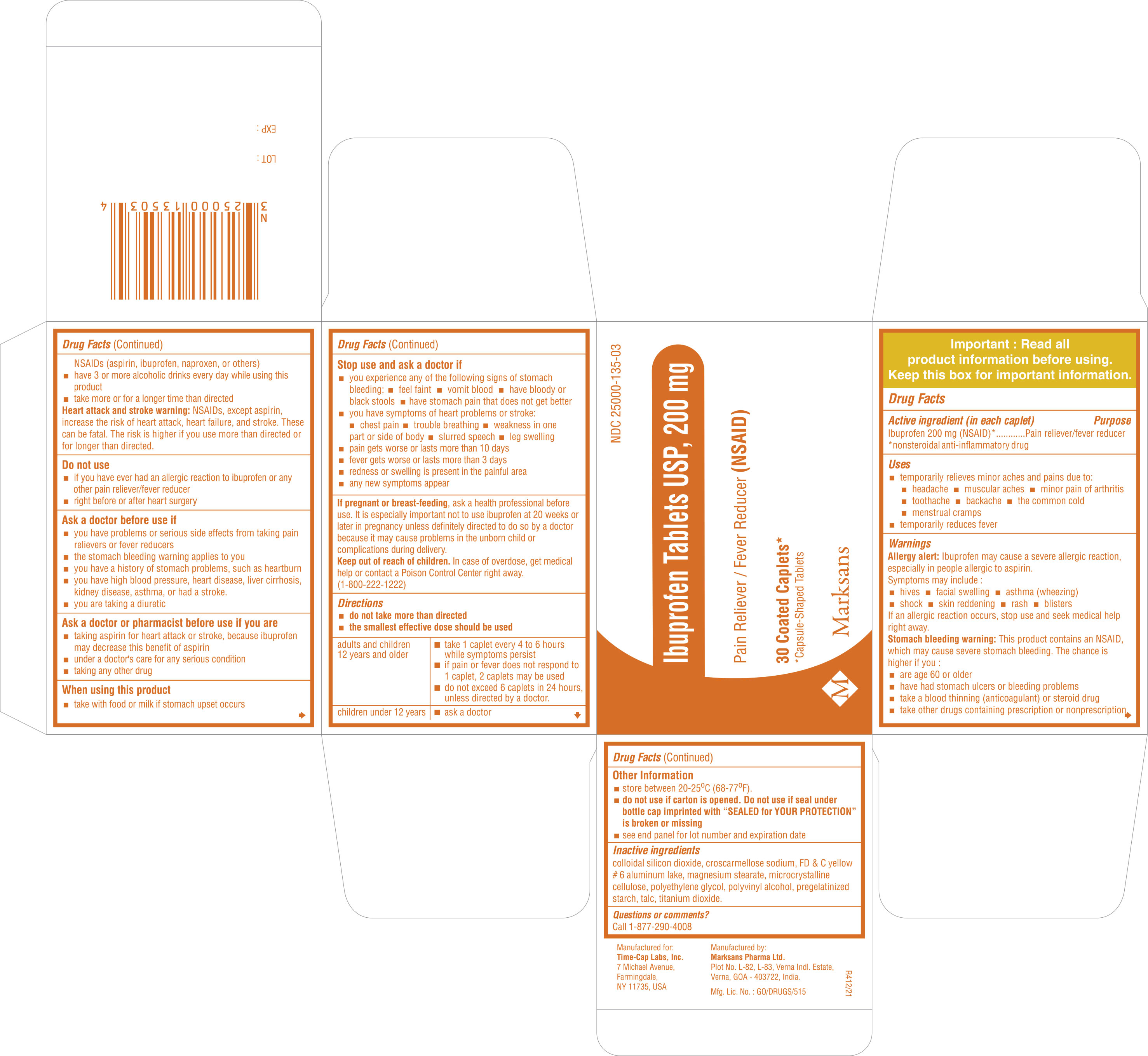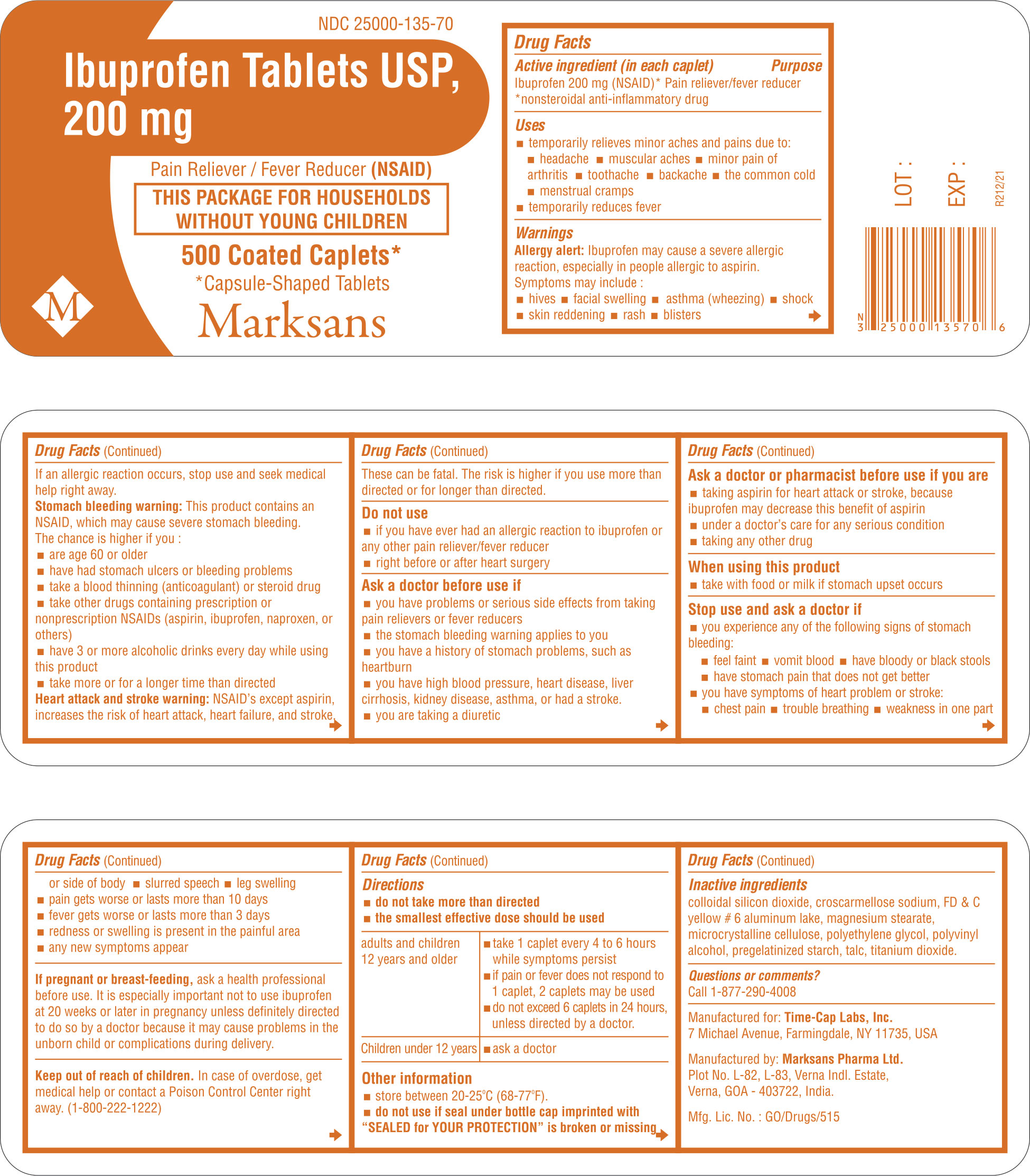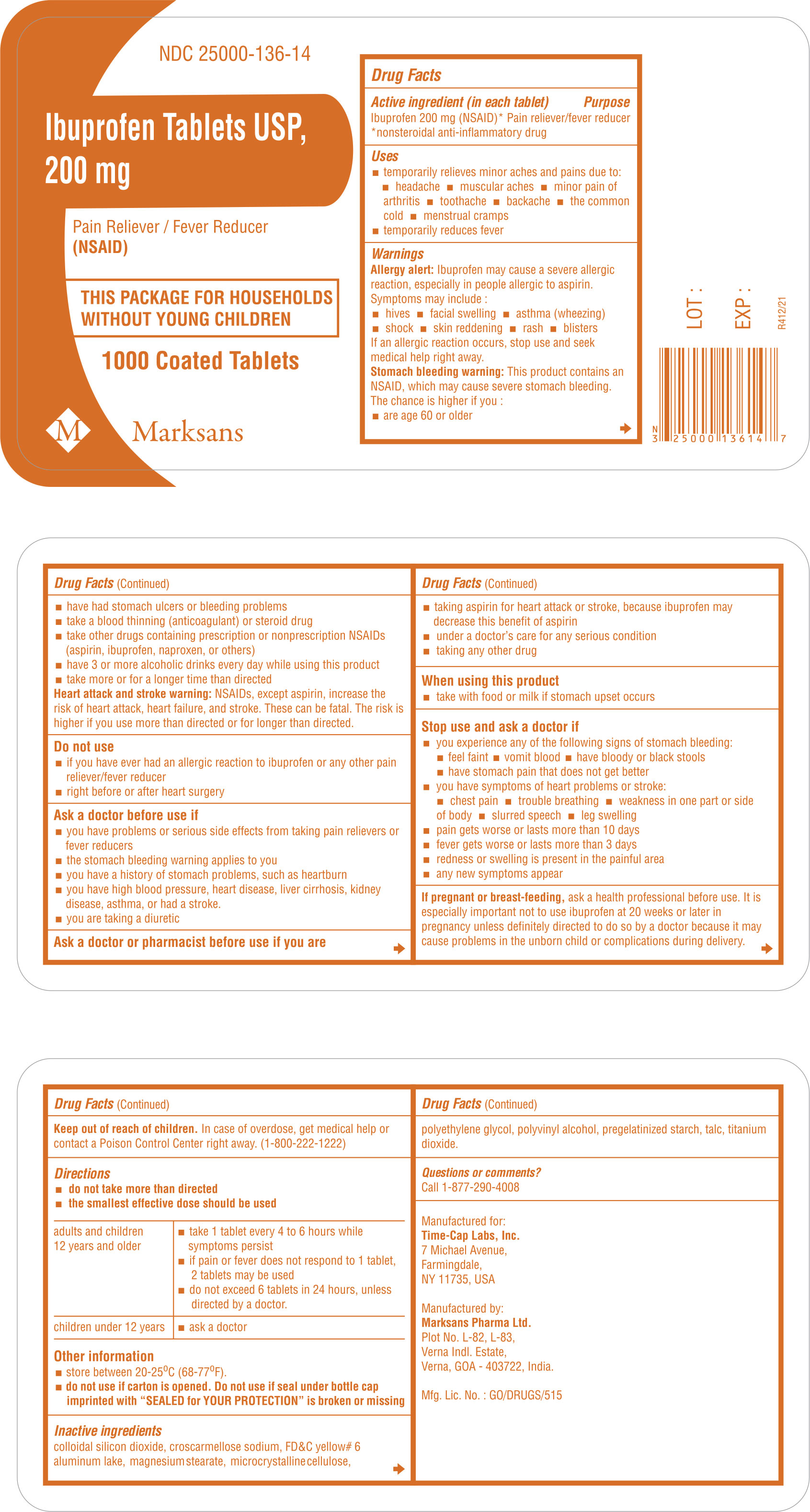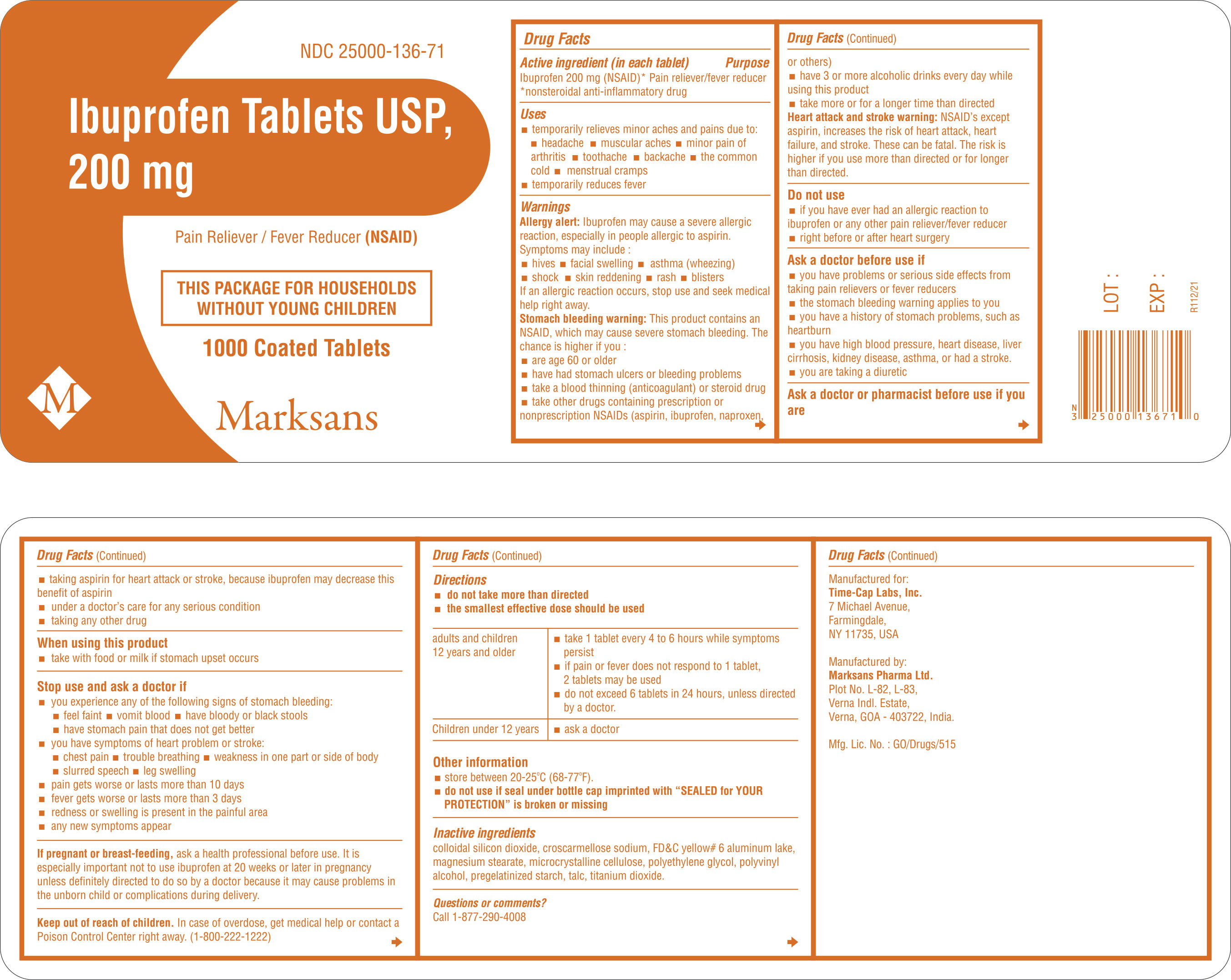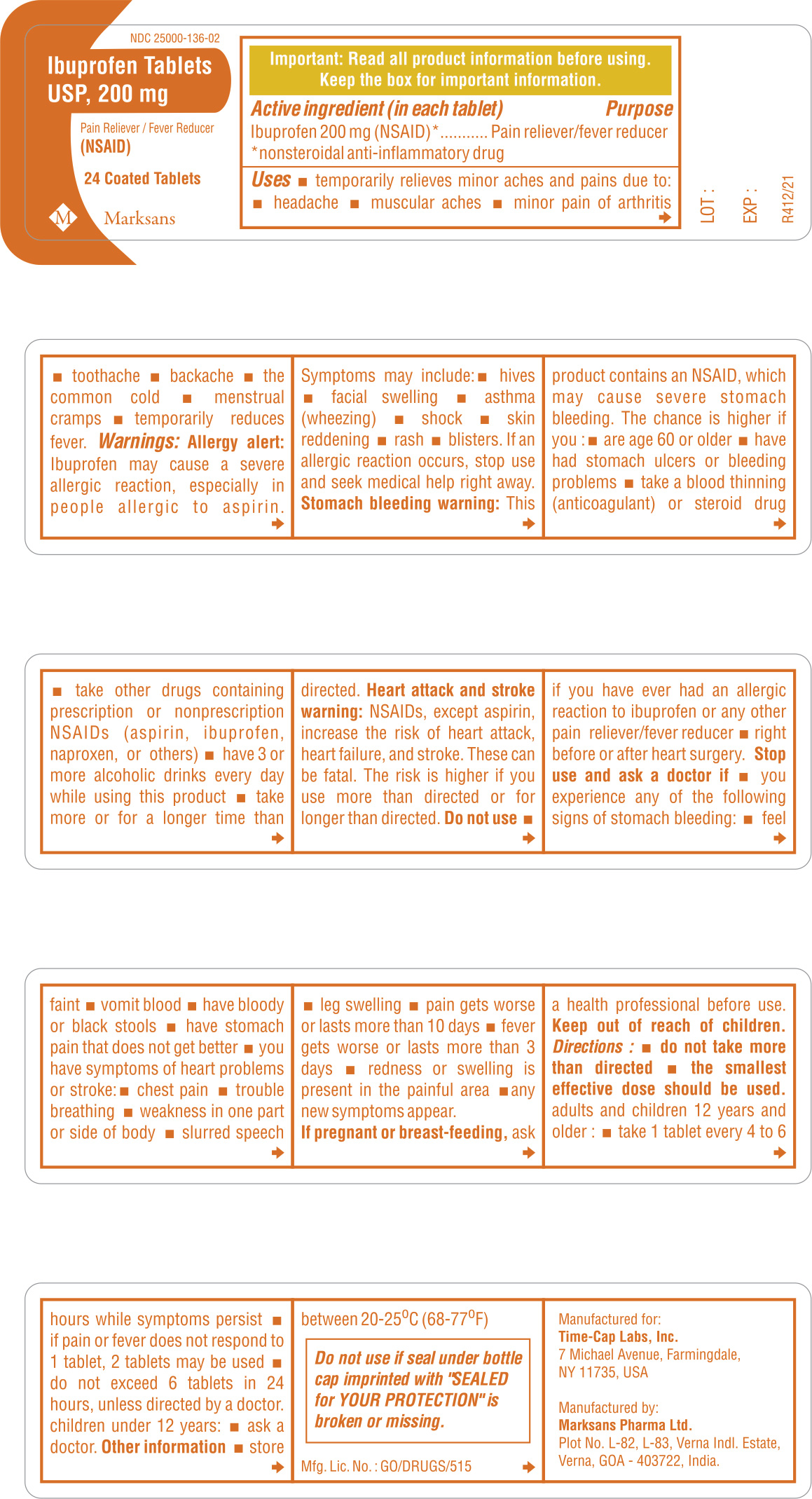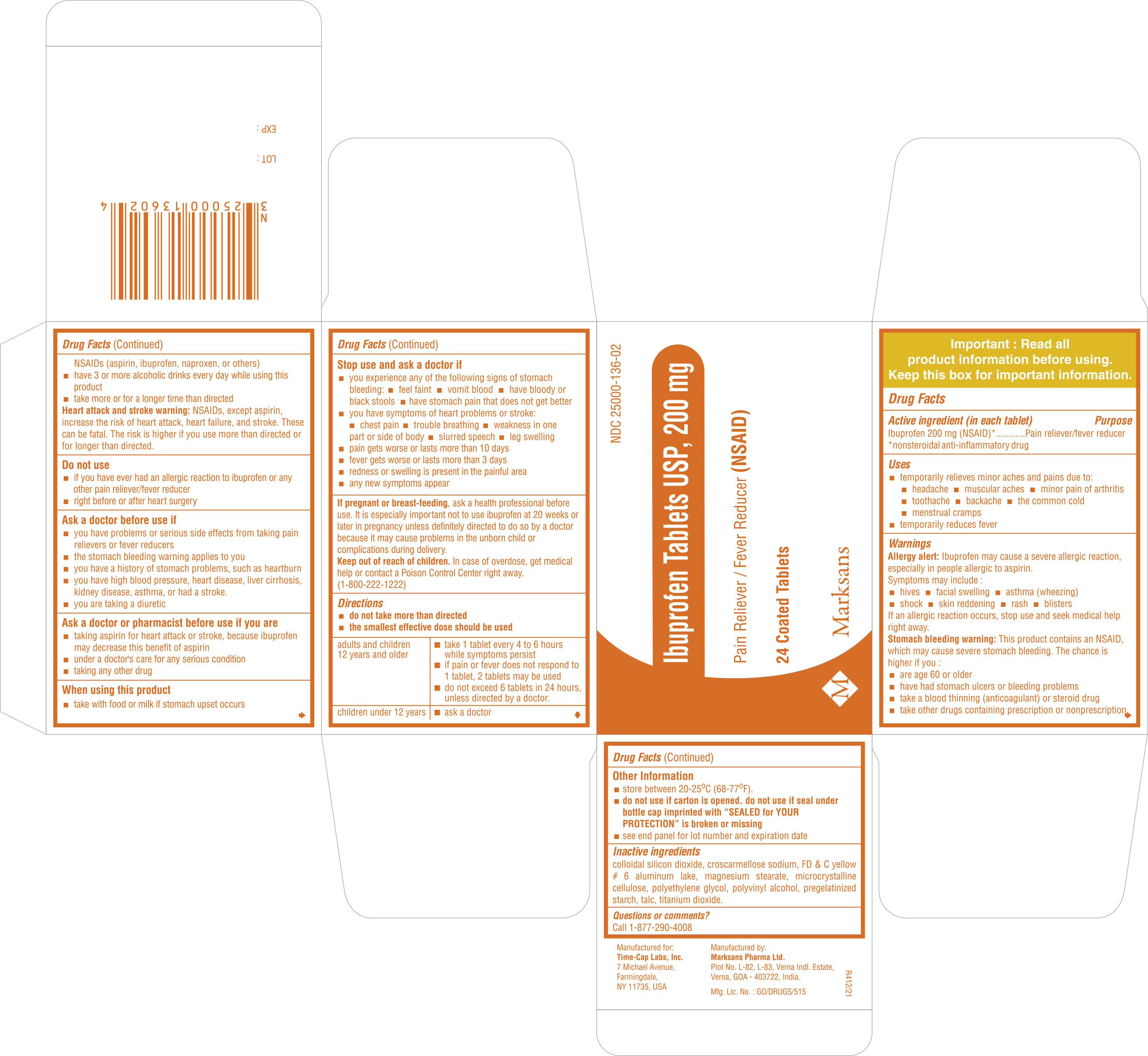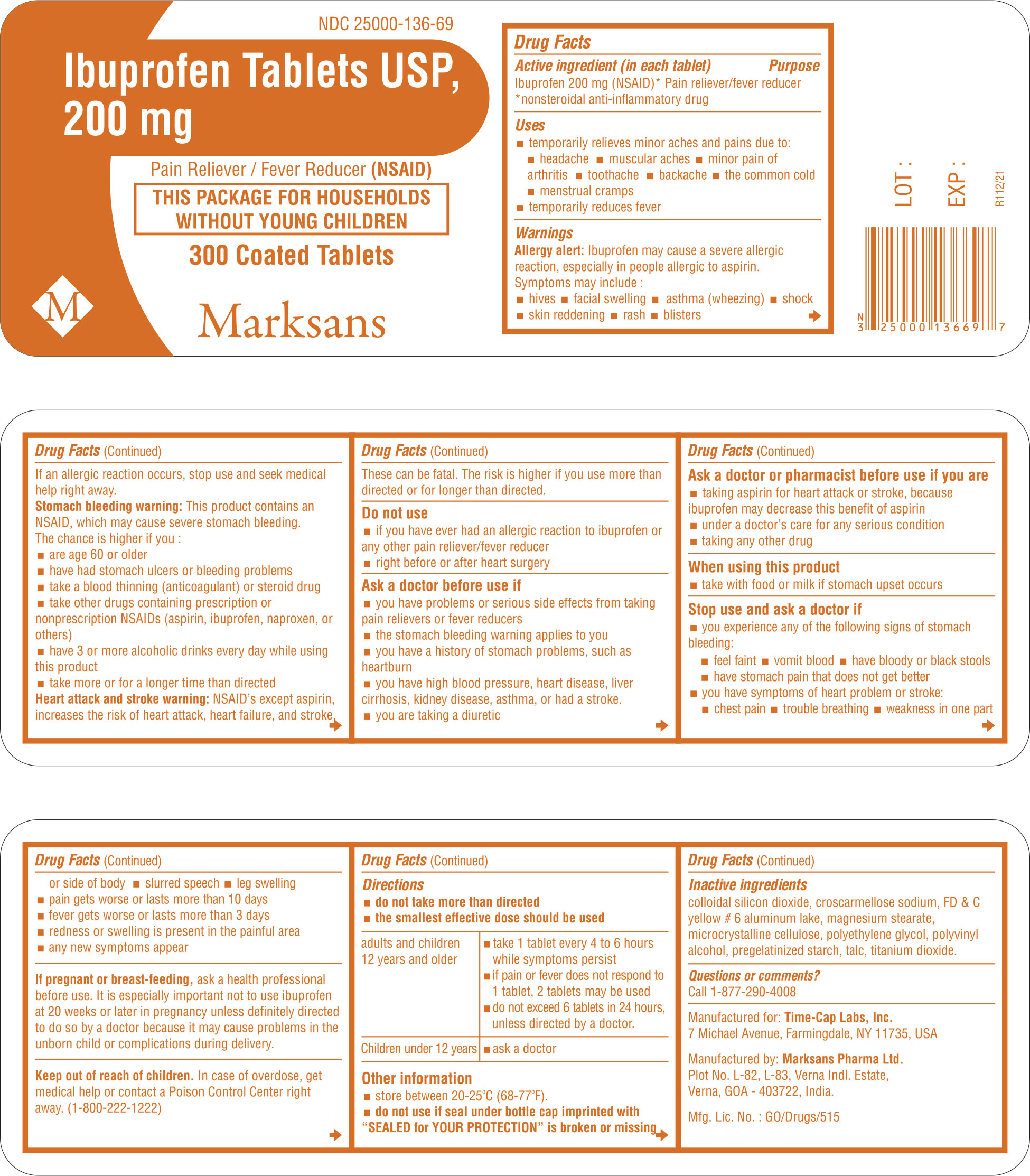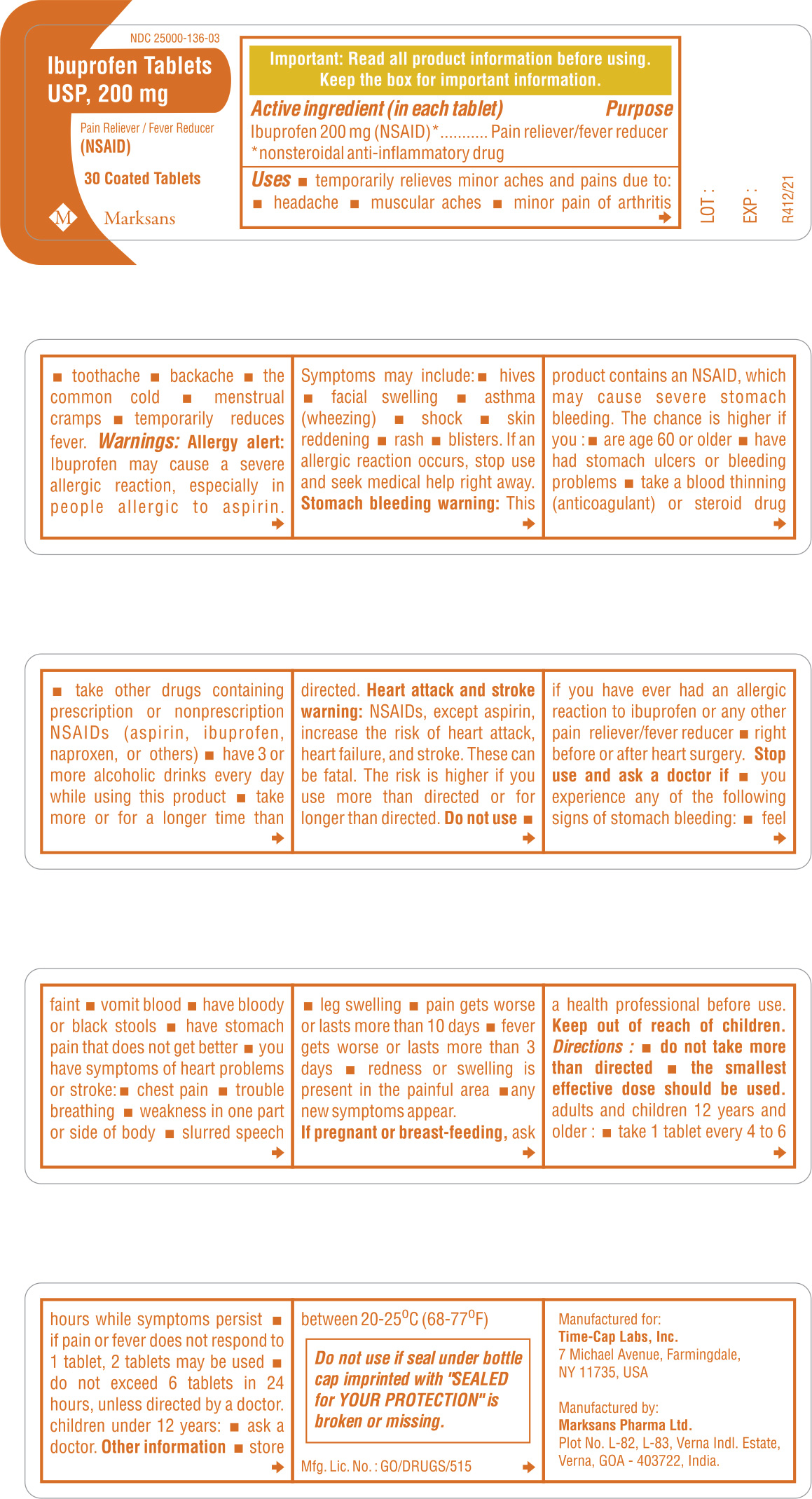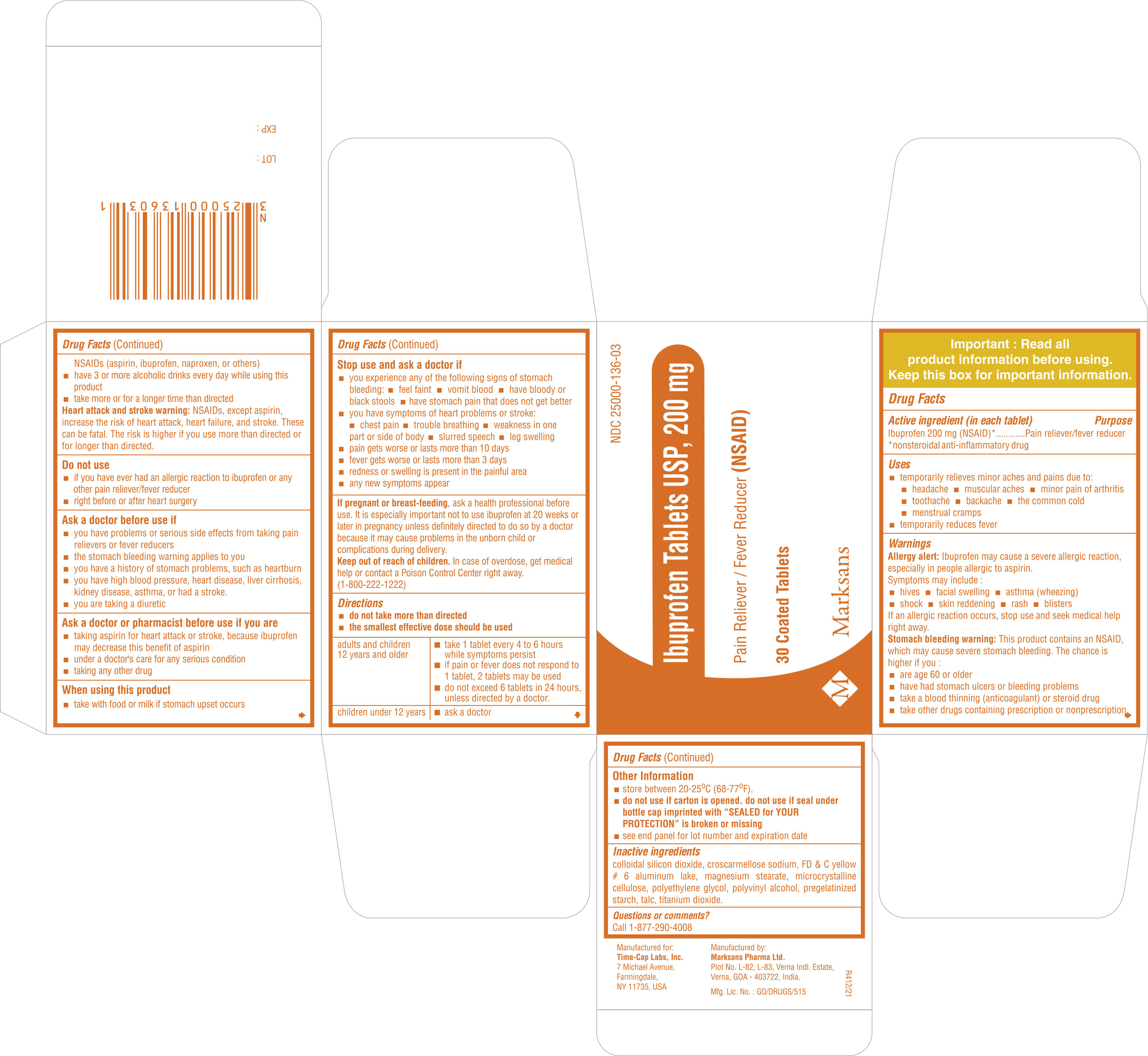 DRUG LABEL: Ibuprofen
NDC: 25000-135 | Form: TABLET
Manufacturer: MARKSANS PHARMA LIMITED
Category: otc | Type: Human OTC Drug Label
Date: 20211221

ACTIVE INGREDIENTS: IBUPROFEN 200 mg/1 1
INACTIVE INGREDIENTS: CELLULOSE, MICROCRYSTALLINE; CROSCARMELLOSE SODIUM; STARCH, PREGELATINIZED CORN; TALC; SILICON DIOXIDE; MAGNESIUM STEARATE; POLYVINYL ALCOHOL; POLYETHYLENE GLYCOL 3350; FD&C YELLOW NO. 6; TITANIUM DIOXIDE

Ibuprofen Tablets 200mg (Orange-Round and Capsule shaped)

Active ingredient(s)

Ibuprofen 200 mg (NSAID)*

*nonsteroidal anti-inflammatory drug

Purpose

Pain reliever/fever reducer

Use(s)

- temporarily relieves minor aches and pains due to:
  - headache
  - muscular aches
  - minor pain of arthritis
  - toothache
  - backache
  - the common cold
  - menstrual cramps
- temporarily reduces fever

Warnings

Allergy alert: Ibuprofen may cause a severe allergic reaction, especially in people allergic to aspirin. Symptoms may include:
• hives
• facial swelling
• asthma (wheezing)
• shock
• skin reddening
• rash
• blisters
If an allergic reaction occurs, stop use and seek medical help right away.

Stomach bleeding warning: This product contains an NSAID, which may cause severe stomach bleeding. The chance is higher if you:
• are age 60 or older
• have had stomach ulcers or bleeding problems
• take a blood thinning (anticoagulant) or steroid drug
• take other drugs containing prescription or nonprescription NSAIDs [aspirin, ibuprofen, naproxen, or others]
• have 3 or more alcoholic drinks every day while using this product
• take more or for a longer time than directed

Heart attack and stroke warning: NSAIDs, except aspirin, increase the risk of heart attack, heart failure, and stroke. These can be fatal. The risk is higher if you use more than directed or for longer than directed.

Do not use

- if you have ever had an allergic reaction to ibuprofen or any other pain reliever/fever reducer
- right before or after heart surgery

Ask a doctor before use if

- you have problems or serious side effects from taking pain relievers or fever reducers
- the stomach bleeding warning applies to you
- you have a history of stomach problems, such as heartburn
- you have high blood pressure, heart disease, liver cirrhosis, or kidney disease, asthma, or had a stroke.
- you are taking a diuretic

Ask a doctor or pharmacist before use if

- taking aspirin for heart attack or stroke, because ibuprofen may decrease this benefit of aspirin
- under a doctor’s care for any serious condition
- taking any other drug

When using this product

- take with food or milk if stomach upset occurs

Stop use and ask doctor if

- you experience any of the following signs of stomach bleeding:
  - feel faint
  - vomit blood
  - have bloody or black stools
  - have stomach pain that does not get better
- you have symptoms of heart problems or stroke:
  - chest pain
  - trouble breathing
  - weakness in one part or side of body
  - slurred speech
  - leg swelling
- pain gets worse or lasts more than 10 days
- fever gets worse or lasts more than 3 days
- redness or swelling is present in painful area
- any new symptoms appear

If pregnant or breast-feeding

ask a health professional before use. It is especially important not to use ibuprofen at 20 weeks or later in pregnancy unless definitely directed to do so by a doctor because it may cause a problems in the unborn child or complications during delivery.

Keep out of reach of children

In case of overdose, get medical help or contact a Poison Control Center right away. (1-800-222-1222)

Directions

- do not take more than directed
- the smallest effective dose should be used

adults and children 12 years and older | - take 1 tablet every 4 to 6 hours while symptoms persist - if pain or fever does not respond to 1 tablet, 2 tablets may be used - do not exceed 6 tablets in 24 hours, unless directed by a doctor.
children under 12 years | - ask a doctor

Other information

- store at 20-25ºC (68-77ºF)

- do not use if carton is opened. Do not use if seal under bottle cap imprinted with "SEALED for YOUR PROTECTION" is broken or missing
- see end panel for lot number and expiration date

Inactive ingredient(s)

colloidal silicon dioxide, croscarmellose sodium, FD & C yellow # 6 aluminum lake, magnesium stearate, microcrystalline cellulose, polyethylene glycol, polyvinyl alcohol, pregelatinized starch, talc, titanium dioxide.

Questions or comments?
Call 1-877-290-4008

Manufactured for:

Time-Cap Labs, Inc.

7 Michael Avenue,

Farmingdale,

NY 11735, USA

Manufactured by:

Marksans Pharma Ltd.

Plot No. L-82, L-83,
Verna Indl. Estate,
Verna, Goa-403 722, India.

Principal Display Panel

NDC 25000-136-03, Ibuprofen Tablets, USP 200mg

30 counts Bottle Label

NDC 25000-136-03,Ibuprofen Tablets, USP 200mg

30 counts Carton Label

NDC 25000-135-03, Ibuprofen Tablets, USP 200mg (Caplets)

30 counts Bottle Label

NDC 25000-135-03, Ibuprofen Tablets, USP 200mg (Caplets)

30 counts Carton Label

NDC 25000-136-69, Ibuprofen Tablets, USP 200mg

300 counts Bottle Label

NDC 25000-136-14, Ibuprofen Tablets, USP 200mg

1000 counts Bottle Label

NDC 25000-136-71, Ibuprofen Tablets, USP 200mg

1000 counts (PET) Bottle Label

NDC 25000-135-14, Ibuprofen Tablets, USP 200mg (Caplets)

1000 counts Bottle Label

NDC 25000-135-70, Ibuprofen Tablets, USP 200mg (Caplets)

500 counts Bottle Label

NDC 25000-136-02, Ibuprofen Tablets, USP 200mg

24 counts Bottle Label

NDC 25000-136-02, Ibuprofen Tablets, USP 200mg

24 counts Carton Label

NDC 25000-135-02, Ibuprofen Tablets, USP 200mg (Caplets)

24 counts Bottle Label

NDC 25000-135-02, Ibuprofen Tablets, USP 200mg (Caplets)

24 counts Carton Label